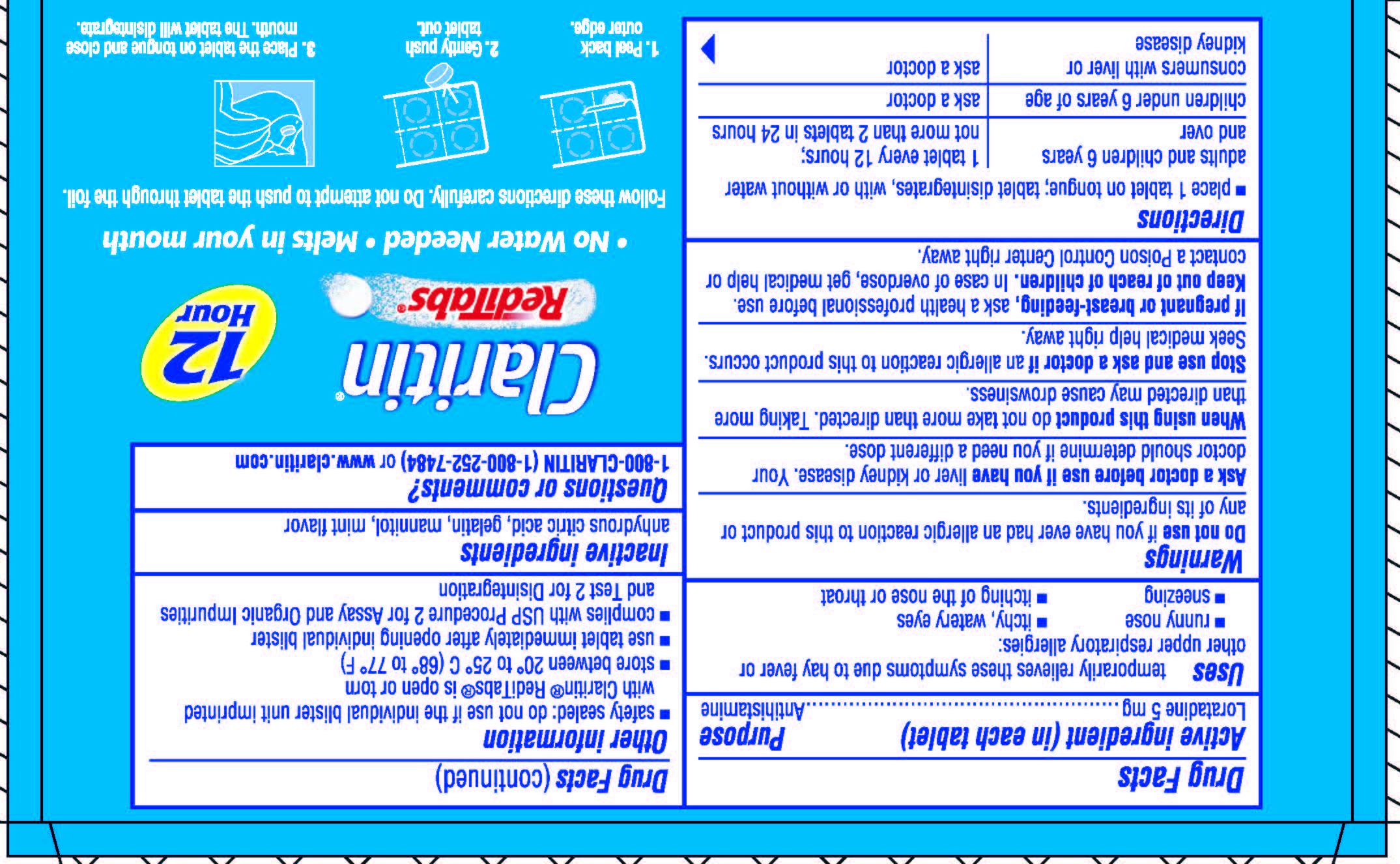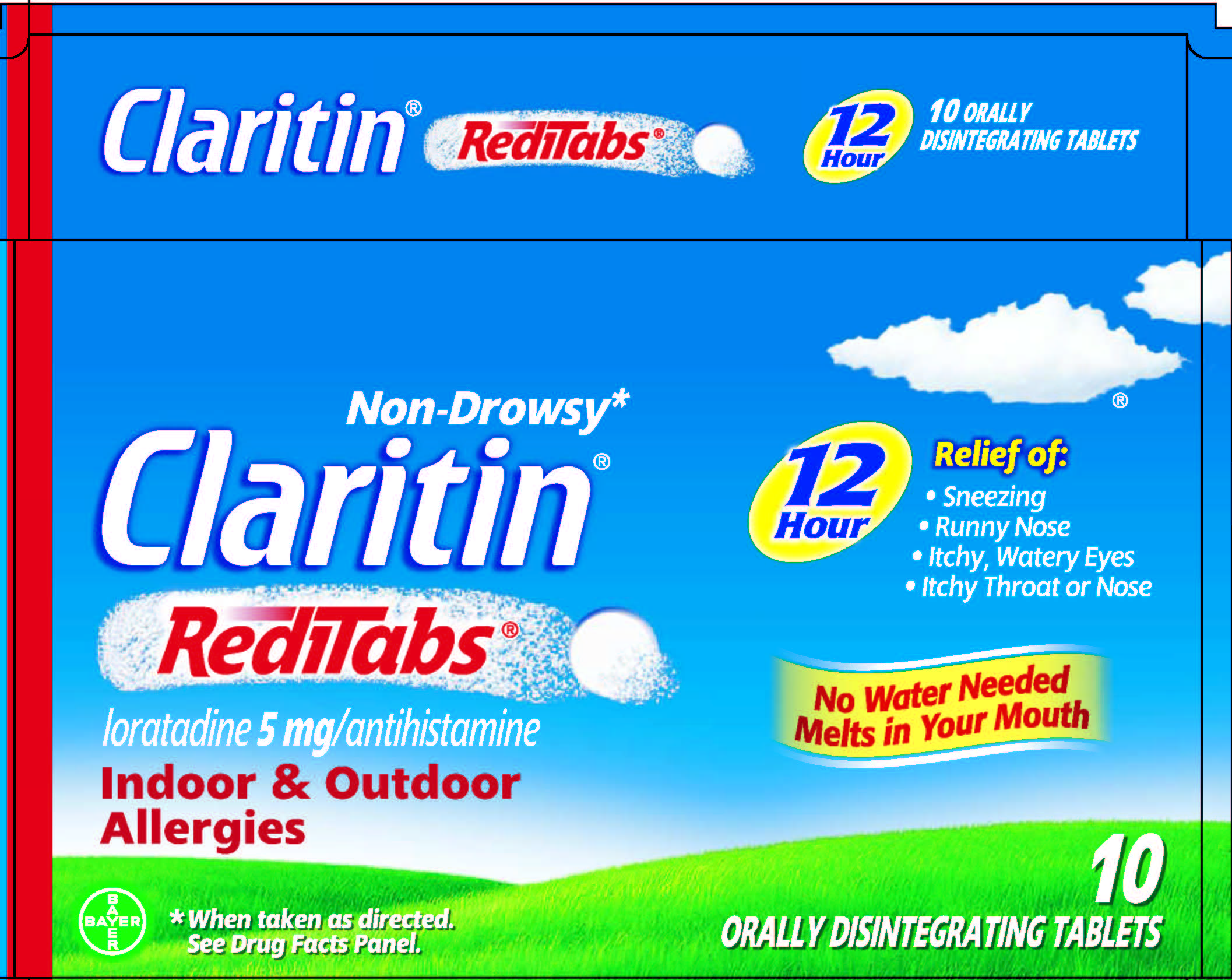 DRUG LABEL: Claritin
NDC: 11523-7202 | Form: TABLET, ORALLY DISINTEGRATING
Manufacturer: Bayer HealthCare LLC
Category: otc | Type: HUMAN OTC DRUG LABEL
Date: 20251205

ACTIVE INGREDIENTS: LORATADINE 5 mg/1 1
INACTIVE INGREDIENTS: ANHYDROUS CITRIC ACID; GELATIN; MANNITOL

Claritin®
RediTabs®

Drug Facts

Active ingredient (in each tablet)

Loratadine 5 mg

Purpose

Antihistamine

Uses

temporarily relieves these symptoms due to hay fever or other upper respiratory allergies:

- runny nose
- itchy, watery eyes
- sneezing
- itching of the nose or throat

Warnings

Do not use if you have ever had an allergic reaction to this product or any of its ingredients.

Ask a doctor before use if you have liver or kidney disease. Your doctor should determine if you need a different dose.

When using this product do not take more than directed. Taking more than directed may cause drowsiness.

Stop use and ask a doctor if an allergic reaction to this product occurs. Seek medical help right away.

PREGNANCY OR BREAST FEEDING

If pregnant or breast-feeding, ask a health professional before use.

Keep out of reach of children. In case of overdose, get medical help or contact a Poison Control Center right away.

Directions

- place 1 tablet on tongue; tablet disintegrates, with or without water

adults and children 6 years and over | 1 tablet every 12 hours; not more than 2 tablets in 24 hours
children under 6 years of age | ask a doctor
consumers with liver or kidney disease | ask a doctor

Other information

- safety sealed: do not use if the individual blister unit imprinted with Claritin® RediTabs® is open or torn
- store between 20° to 25°C (68° to 77°F)
- use tablet immediately after opening individual blister
- complies with USP Procedure 2 for Assay and Organic Impurities and Test 2 for Disintegration

Inactive ingredients

anhydrous citric acid, gelatin, mannitol, mint flavor

Questions or comments?

1-800-CLARITIN (1-800-252-7484) or www.claritin.com

Distributed by MSD Consumer Care, Inc.,
PO Box 377, Memphis, TN 38151 USA,
a subsidiary of Merck & Co., Inc., Whitehouse Station, NJ USA.

PRINCIPAL DISPLAY PANEL - 10 Tablet Carton

NDC 11523-7202-3

Non-Drowsy*
Claritin®
RediTabs®
loratadine 5 mg/antihistamine

Indoor & Outdoor
Allergies

*When taken as directed. See Drug Facts Panel.

12
Hour

Relief of:

- Sneezing
- Runny Nose
- Itchy, Watery Eyes
- Itchy Throat
  or Nose

No Water Needed
Melts in Your Mouth

10
ORALLY
DISINTEGRATING TABLETS